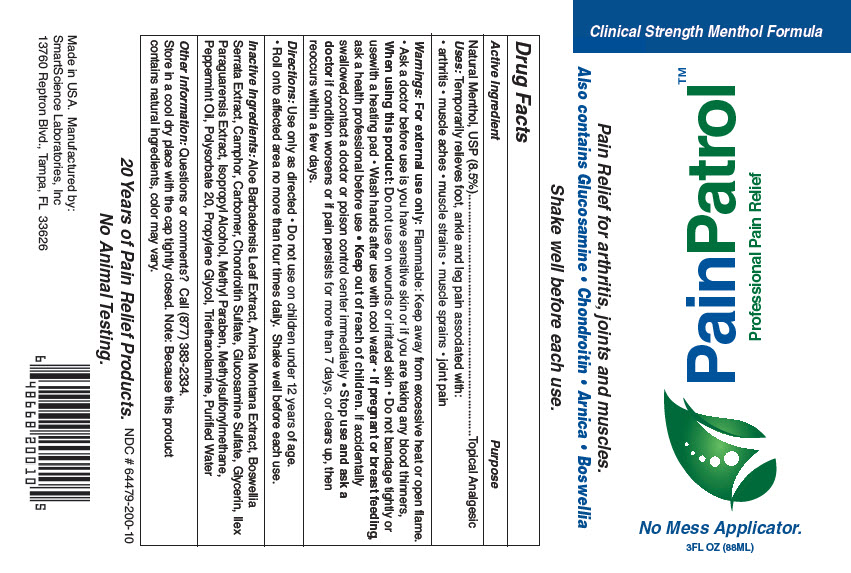 DRUG LABEL: PainPatrol Professional Pain Relief
NDC: 64479-200 | Form: GEL
Manufacturer: SmartScience Laboratories, Inc.
Category: otc | Type: HUMAN OTC DRUG LABEL
Date: 20200219

ACTIVE INGREDIENTS: Menthol, Unspecified Form 85 mg/1 mL
INACTIVE INGREDIENTS: ALOE VERA LEAF; ARNICA MONTANA; INDIAN FRANKINCENSE; CAMPHOR (SYNTHETIC); CARBOMER INTERPOLYMER TYPE A (ALLYL SUCROSE CROSSLINKED); CHONDROITIN SULFATE (SHARK); GLUCOSAMINE SULFATE POTASSIUM CHLORIDE; GLYCERIN; ILEX PARAGUARIENSIS LEAF; ISOPROPYL ALCOHOL; METHYLPARABEN; DIMETHYL SULFONE; PEPPERMINT OIL; POLYSORBATE 20; PROPYLENE GLYCOL; TROLAMINE; WATER

PainPatrol™ Professional Pain Relief

Drug Facts

Active Ingredient

Natural Menthol, USP (8.5%)

Purpose

Topical Analgesic

Uses

Temporarily relieves foot, ankle and leg pain associated with:

- arthritis
- muscle aches
- muscle strains
- muscle sprains
- joint pain

Warnings

For external use only: Flammable: Keep away from excessive heat or open flame.

- Ask a doctor before use is you have sensitive skin or if you are taking any blood thinners,

When using this product

Do not use on wounds or irritated skin

- Do not bandage tightly or usewith a heating pad
- Wash hands after use with cool water

PREGNANCY OR BREAST FEEDING

- If pregnant or breast feeding, ask a health professional before use

- Keep out of reach of children. If accidentally swallowed,contact a doctor or poison control center immediately

- Stop use and ask a doctor if condition worsens or if pain persists for more than 7 days, or clears up, then reoccurs within a few days.

Directions

Use only as directed

- Do not use on children under 12 years of age.
- Roll onto affected area no more than four times daily. Shake well before each use.

Inactive Ingredients

Aloe Barbadensis Leaf Extract, Arnica Montana Extract, Boswellia Serrata Extract, Camphor, Carbomer, Chondroitin Sulfate, Glucosamine Sulfate, Glycerin, Ilex Paraguarensis Extract, Isopropyl Alcohol, Methyl Paraben, Methylsulfonylmethane, Peppermint Oil, Polysorbate 20, Propylene Glycol, Triethanolamine, Purified Water

Other Information

Questions or comments?

Call (877) 383-2334.

STORAGE AND HANDLING

Store in a cool dry place with the cap tightly closed. Note: Because this product contains natural ingredients, color may vary.

Manufactured by:
SmartScience Laboratories, Inc
13760 Reptron Blvd., Tampa, FL 33626

PRINCIPAL DISPLAY PANEL - 88 ML Bottle Label

Clinical Strength Menthol Formula

PainPatrol™
Professional Pain Relief

Pain Relief for arthritis, joints and muscles.
Also contains Glucosamine • Chondroitin • Arnica • Boswellia

No Mess Applicator.
3FL OZ (88ML)